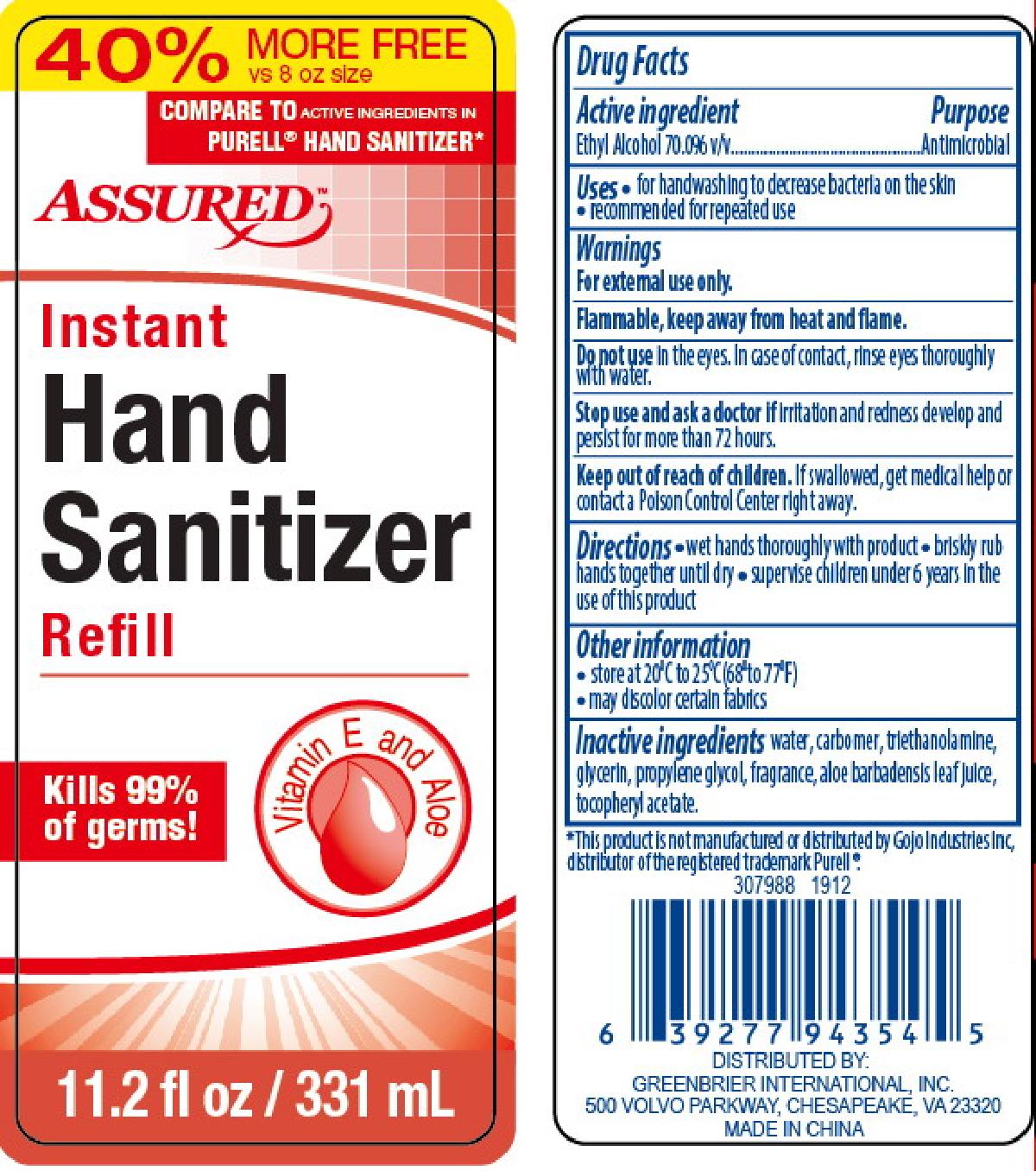 DRUG LABEL: Assured Instant Hand Sanitizer Refill 11.2oz
NDC: 33992-3039 | Form: GEL
Manufacturer: Greenbrier International, Inc.
Category: otc | Type: HUMAN OTC DRUG LABEL
Date: 20200203

ACTIVE INGREDIENTS: ALCOHOL 70 mL/100 mL
INACTIVE INGREDIENTS: ALPHA-TOCOPHEROL ACETATE; WATER; CARBOMER COPOLYMER TYPE A; TROLAMINE; GLYCERIN; PROPYLENE GLYCOL; ALOE VERA LEAF

Assured Instant Hand Sanitizer Refill 11.2 oz

Active Ingredient Purpose

Ethyl Alcohol 70.0% v/v..................... Antimicrobial

PURPOSE

Antimicrobial

Keep out of reach of children. If swallowed, get medical help or contact a Poison Control Center right away.

Uses

- for handwashing to decrease bacteria on the skin
- recommended for repeated use

Directions

- wet hands thoroughly with product
- briskly rub hands together until dry
- supervise children under 6 years in the use of this product

Warnings

For external use only.

Flammable, keep away from heat and flame.

Do not use in the eyes. In case of contact, rinse eyes thoroughly with water.

Inactive Ingredients

water, carbomer, triethanolamine, glycerin, propylene glycol, fragrance, aloe barbadensis leaf juice, tocopheryl acetate

Stop use and ask a doctor if irritation and redness develop and persist for more than 72 hours.

Other Information

- store at 20C to 25C (68F to 77F)
- may discolor certain fabrics